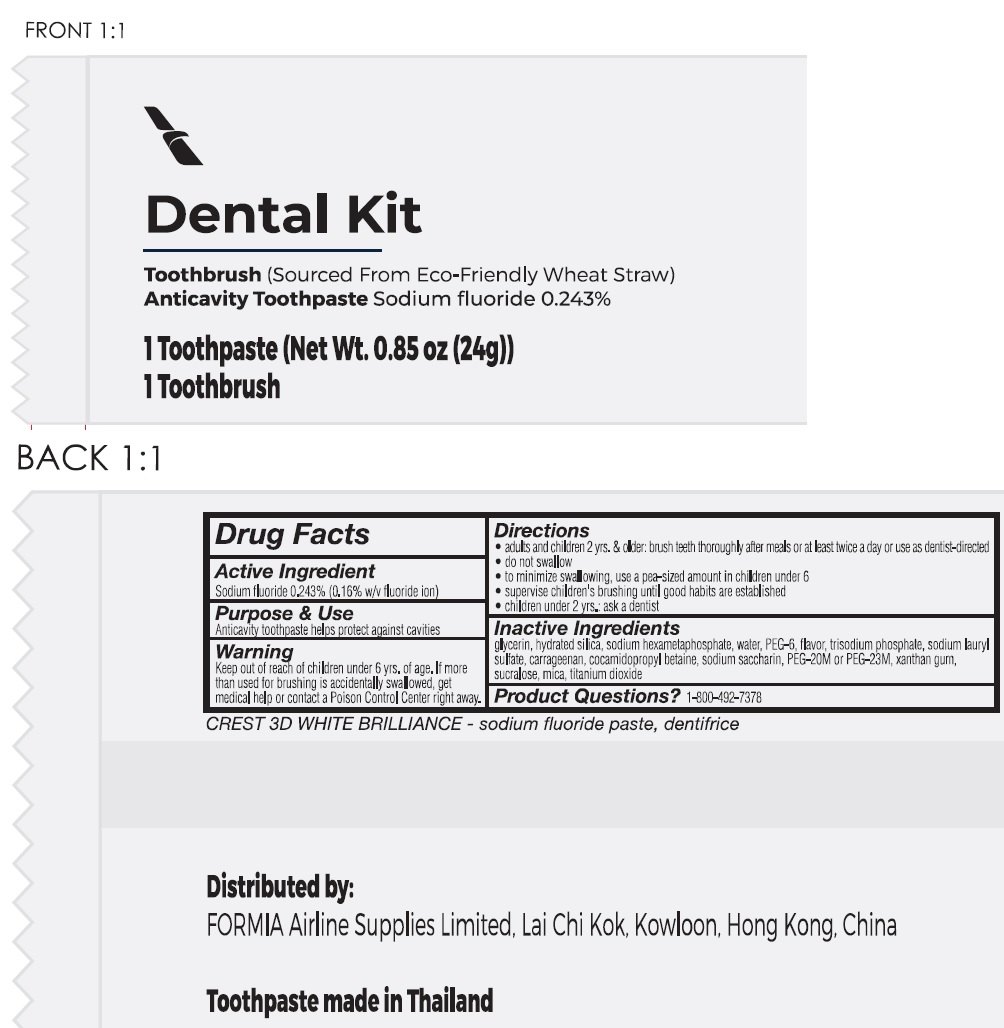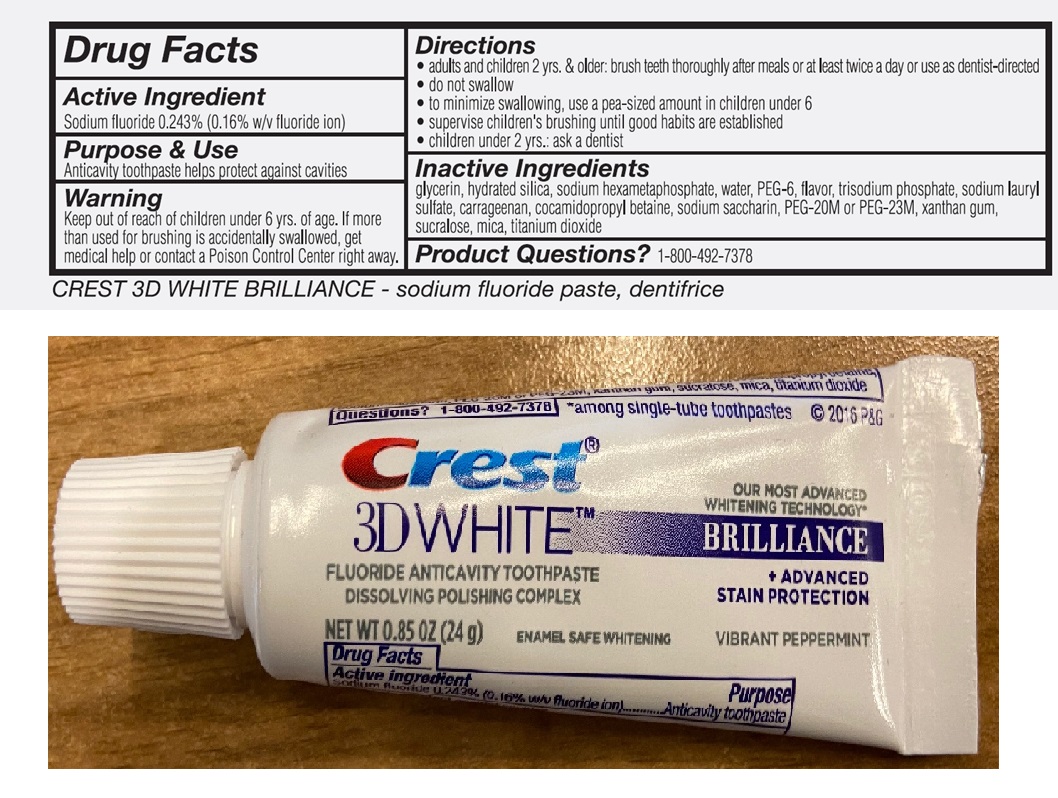 DRUG LABEL: Crest 24g and Toothbrush Dental kit
NDC: 79940-007 | Form: KIT | Route: DENTAL
Manufacturer: Formia Airline Supplies Limited
Category: otc | Type: HUMAN OTC DRUG LABEL
Date: 20231031

ACTIVE INGREDIENTS: SODIUM FLUORIDE 1.6 mg/1 g
INACTIVE INGREDIENTS: GLYCERIN; HYDRATED SILICA; HEXASODIUM HEXAMETAPHOSPHATE; WATER; POLYETHYLENE GLYCOL 300; METHYL SALICYLATE; SODIUM LAURYL SULFATE; CARRAGEENAN; COCAMIDOPROPYL BETAINE; SACCHARIN SODIUM; POLYETHYLENE OXIDE 900000; XANTHAN GUM; SUCRALOSE; MICA; TITANIUM DIOXIDE

Crest 24g Toothpaste and Toothbrush Dental kit

Active Ingredient

Sodium fluoride 0.243% (0.16% w/v fluoride ion)

Purpose

Acticavity

Use

toothpate helps protect against cavities

Warning

Keep out of reach of children

under 6 yrs. of age. If more than used for brushing is accidentally swallowed, get medical help or contact a Poison Control Center right away.

Directions

- adults and children 2 yrs. & older: brush teeth thoroughly after meals or at least twice a day or use as dentist-directed
- do not swallow
- to minimize swallowing, use a pea-sized amount in children under 6
- supervise children's brushing until good habits are established
- children under 2 yrs: ask a dentist

Inactive Ingredients

glycerin, hydrated silica, sodium hexametaphosphate, water, PEG-6, flavor, trisodium phosphate, sodium lauryl sulfate, carrageenan, cocamidopropyl betaine, sodium saccharin, PEG-20M, xanthan gum, sucralose, mica, titanium dioxide

Product Questions?

1-800-492-7378